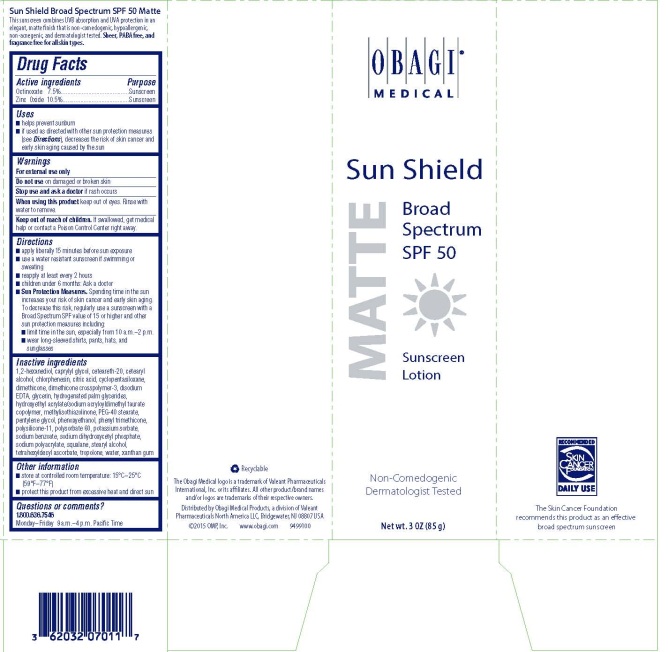 DRUG LABEL: SUN SHIELD BROAD SPECTRUM SPF 50 MATTE
NDC: 62032-125 | Form: LOTION
Manufacturer: OMP, Inc.
Category: otc | Type: HUMAN OTC DRUG LABEL
Date: 20160805

ACTIVE INGREDIENTS: OCTINOXATE 75 mg/1 g; ZINC OXIDE 105 mg/1 g
INACTIVE INGREDIENTS: WATER; GLYCERIN; PHENOXYETHANOL; XANTHAN GUM; CHLORPHENESIN; CYCLOMETHICONE 5; PENTYLENE GLYCOL; PHENYL TRIMETHICONE; HYDROXYETHYL ACRYLATE/SODIUM ACRYLOYLDIMETHYL TAURATE COPOLYMER (45000 MPA.S AT 1%); SQUALANE; POLYSORBATE 60; PEG-40 STEARATE; DIMETHICONE; STEARYL ALCOHOL; CETOSTEARYL ALCOHOL; SODIUM DIHYDROXYCETYL PHOSPHATE; HYDROGENATED PALM GLYCERIDES; POLYOXYL 20 CETOSTEARYL ETHER; 1,2-HEXANEDIOL; CAPRYLYL GLYCOL; TROPOLONE; CITRIC ACID MONOHYDRATE; EDETATE DISODIUM; POTASSIUM SORBATE; SODIUM BENZOATE; METHYLISOTHIAZOLINONE; TETRAHEXYLDECYL ASCORBATE

Sun Shield Broad Spectrum SPF 50 MATTE
Sunscreen Lotion

Active ingredients

Octinoxate 7.5%, Zinc Oxide 10.5%

Purpose

Sunscreen

Uses

- helps prevent sunburn
- if used as directed with other sun protection measures (see Directions), decreases the risk of skin cancer and early skin aging caused by the sun

Warnings

For external use only

Do not use on damaged or broken skin

Stop use and ask a doctor if rash occurs

When using this product keep out of eyes. Rinse with water to remove.

Keep out of reach of children. If swallowed, get medical help or contact a Poison Control Center right away.

Directions

- apply liberally 15 minutes before sun exposure.
- use a water resistant sunscreen if swimming or sweating
- reapply at least every 2 hours
- children under 6 months: Ask a doctor
- Sun Protection Measures. Spending time in the sun increases your risk of skin cancer and early skin aging. To decrease this risk, regularly use a sunscreen with a Broad Spectrum SPF value of 15 or higher and other sun protection measures including:
  - limit time in the sun, especially from 10 a.m.- 2 p.m.
  - wear long-sleeved shirts, pants, hats, and sunglasses

Inactive ingredients

1,2-hexanediol, caprylyl glycol, ceteareth-20, cetearyl alcohol, chlorphenesin, citric acid, cyclopentasiloxane, dimethicone, dimethicone crosspolymer-3, disodium EDTA, glycerin, hydrogenated palm glycerides, hydroxyethyl acrylate/sodium acryloyldimethyl taurate copolymer, methylisothiazolinone, PEG-40 stearate, pentylene glycol, phenoxyethanol, phenyl trimethicone, polysilicone-11, polysorbate 60, potassium sorbate, sodium benzoate, sodium dihydroxycetyl phosphate, sodium polyacrylate, squalane, stearyl alcohol, tetrahexyldecyl ascorbate, tropolone, water, xanthan gum

Other information

- store at controlled room temperature: 15°C–25°C (59°F–77°F)
- protect this product from excessive heat and direct sun

Questions or comments?

1.800.636.7546

Monday–Friday 9 a.m.–4 p.m. Pacific Time

PRINCIPAL DISPLAY PANEL - 85 g Tube Label

OBAGI®
MEDICAL

Sun Shield

MATTE

Broad
Spectrum
SPF 50

Sunscreen
Lotion

Non-Comedogenic

Dermatologist Tested

Net wt. 3 OZ (85 g)